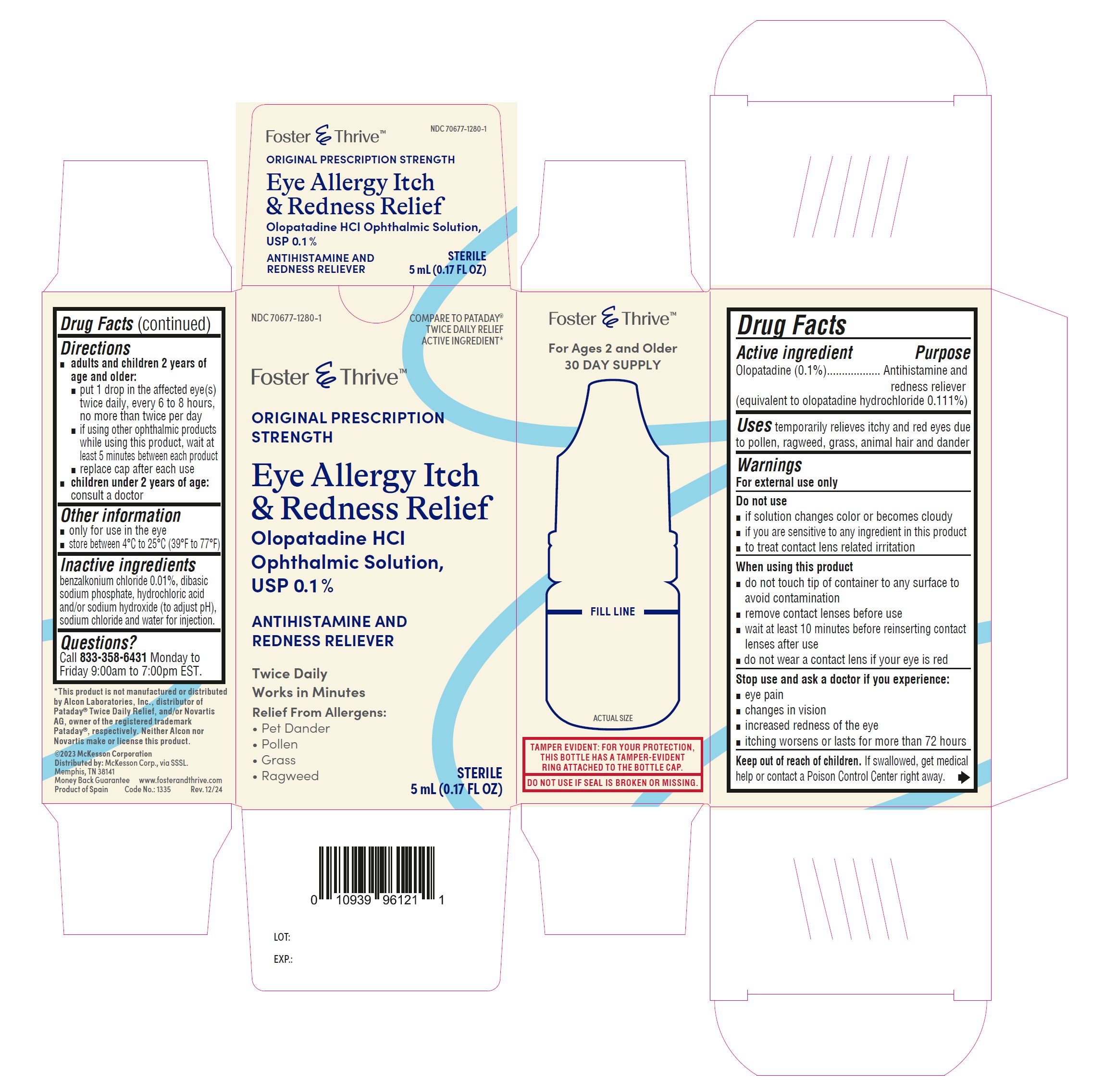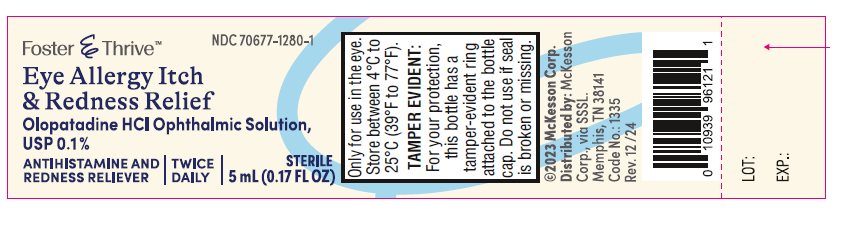 DRUG LABEL: OLOPATADINE HYDROCHLORIDE
NDC: 70677-1280 | Form: SOLUTION
Manufacturer: Strategic Sourcing Services LLC
Category: otc | Type: HUMAN OTC DRUG LABEL
Date: 20250207

ACTIVE INGREDIENTS: OLOPATADINE HYDROCHLORIDE 1 mg/1 mL
INACTIVE INGREDIENTS: BENZALKONIUM CHLORIDE; HYDROCHLORIC ACID; SODIUM CHLORIDE; SODIUM HYDROXIDE; SODIUM PHOSPHATE, DIBASIC, ANHYDROUS; WATER

Drug Facts

ACTIVE INGREDIENT

Active Ingredient | Purpose
Olopatadine (0.1%). (equivalent to olopatadine hydrochloride 0.111%) | Antihistamine and redness reliever

Uses

temporarily relieves itchy and red eyes due to pollen, ragweed, grass, animal hair and dander

Warnings
For external use only

Do not use

- if solution changes color or becomes cloudy
- if you are sensitive to any ingredient in this product
- to treat contact lens related irritation

When using this product

- do not touch tip of container to any surface to avoid contamination
- remove contact lenses before use
- wait at least 10 minutes before reinserting contact lenses after use
- do not wear a contact lens if your eye is red

Stop use and ask a doctor if you experience:

- eye pain
- changes in vision
- increased redness of the eye
- itching worsens or lasts for more than 72 hours

Keep out of reach of children. If swallowed, get medical help or contact a Poison Control Center right away.

Directions

- adults and children 2 years of age and older:
- put 1 drop in the affected eye(s) twice daily, every 6 to 8 hours, no more than twice per day
- if using other ophthalmic products while using this product, wait at least 5 minutes between each product
- replace cap after each use
- children under 2 years of age: consult a doctor

Other information

- only for use in the eye
- store between 4°C to 25°C (39°F to 77°F)

Inactive ingredients

benzalkonium chloride 0.01%, dibasic sodium phosphate, hydrochloric acid and/ or sodium hydroxide (to adjust PH), sodium chloride and water for injection.

Questions or comments?

In the U.S., call Monday to Friday 9:00am to 7:00pm EST.at (833) 358-6431.

Distributed by:

McKesson Corp.,

Via Strategic Sourcing Services LLC.

Memphis, TN 38141

Product of Spain

February 2025

PRINCIPAL DISPLAY PANEL

NDC 70677-1280-1

Olopatadine hydrochloride ophthalmic solution 0.1%
Antihistamine and Redness Reliever

Twice Daily Relief
Eye Allergy Itch & Redness Relief

5 mL
STERILE

NDC 70677-1280-1

Olopatadine hydrochloride ophthalmic solution 0.1%
Antihistamine and Redness Reliever

Twice Daily Relief
Eye Allergy Itch & Redness Relief

5 mL
STERILE